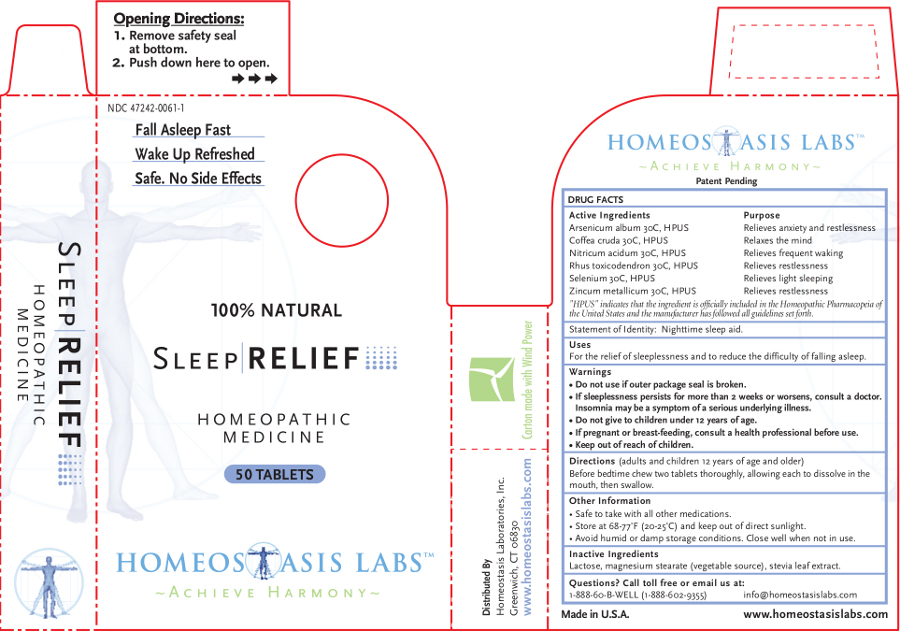 DRUG LABEL: Sleep RELIEF
NDC: 47242-0061 | Form: TABLET, CHEWABLE
Manufacturer: Homeostasis Laboratories, Inc.
Category: homeopathic | Type: HUMAN OTC DRUG LABEL
Date: 20121114

ACTIVE INGREDIENTS: ARSENIC TRIOXIDE 30 [hp_C]/1 1; ARABICA COFFEE BEAN 30 [hp_C]/1 1; NITRIC ACID 30 [hp_C]/1 1; TOXICODENDRON PUBESCENS LEAF 30 [hp_C]/1 1; SELENIUM 30 [hp_C]/1 1; ZINC 30 [hp_C]/1 1
INACTIVE INGREDIENTS: LACTOSE; MAGNESIUM STEARATE; STEVIA REBAUDIUNA LEAF

Sleep RELIEF

Active Ingredients | Purpose
Arsenicum album 30C, HPUS | Relieves anxiety and restlessness
Coffea cruda 30C, HPUS | Relaxes the mind
Nitricum acidum 30C, HPUS | Relieves frequent waking
Rhus toxicodendron 30C, HPUS | Relieves restlessness
Selenium 30C, HPUS | Relieves light sleeping
Zincum metallicum 30C, HPUS | Relieves restlessness

"HPUS" indicates that the ingredient is officially included in the Homeopathic Pharmacopeia of the United States and the manufacturer has followed all guidelines set forth.

Statement of Identity: Nighttime sleep aid.

Uses

For the relief of sleeplessness and to reduce the difficulty of falling asleep.

Warnings

- Do not use if outer package seal is broken.
- If sleeplessness persists for more than 2 weeks or worsens, consult a doctor. Insomnia may be a symptom of a serious underlying illness.
- Do not give to children under 12 years of age.

PREGNANCY OR BREAST FEEDING

- If pregnant or breast-feeding, consult a health professional before use.

- Keep out of reach of children.

Directions

(adults and children 12 years of age and older)

Before bedtime chew two tablets thoroughly, allowing each to dissolve in the mouth, then swallow.

Other information

- Safe to take with all other medications.
- Store at 68-77°F (20-25°C) and keep out of direct sunlight.
- Avoid humid or damp storage conditions. Close well when not in use.

Inactive Ingredients

Lactose, magnesium stearate (vegetable source), stevia leaf extract.

Questions? Call toll free or email us at:

1-888-60-B-WELL (1-888-602-9355)

info@homeostasislabs.com